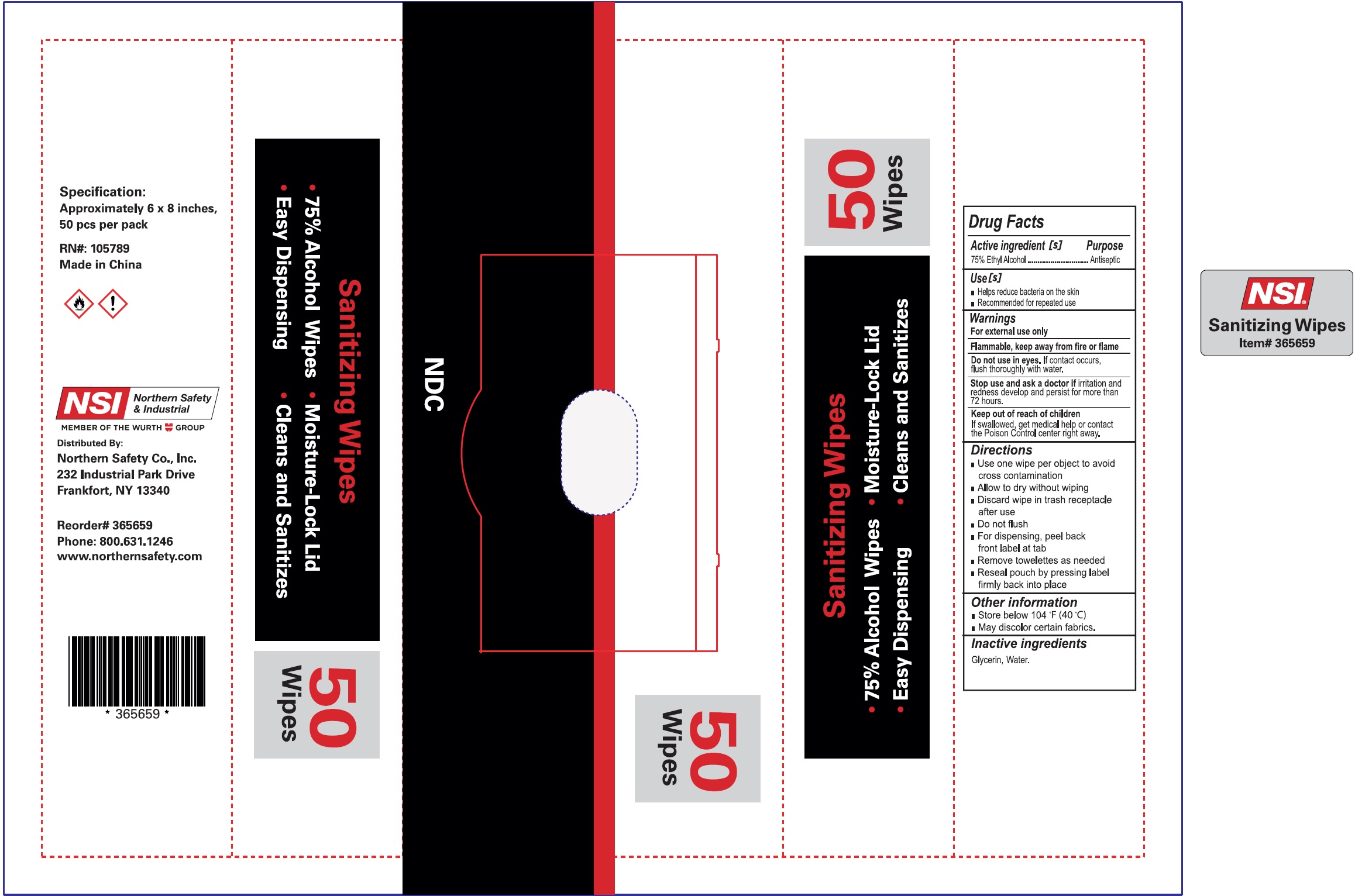 DRUG LABEL: NSI Sanitizing Wipes
NDC: 82716-000 | Form: PATCH
Manufacturer: NORTHERN SAFETY CO., INC.	
Category: otc | Type: HUMAN OTC DRUG LABEL
Date: 20231026

ACTIVE INGREDIENTS: ALCOHOL 75 mL/1 g
INACTIVE INGREDIENTS: GLYCERIN; WATER

NSI Sanitizing Wipes

Active ingredient [s]

75% Ethyl Alcohol

Purpose

Antiseptic

Use [s]

- Helps reduce bacteria on the skin
- Recommended for repeated use

Warnings

For external use only

Flammable, keep away from fire or flame

Do not use

in eyes. If contact occurs, flush thoroughly with water.

Stop use and ask a doctor if

irritation and redness develop and persist for more than 72 hours.

Keep out of reach of children

If swallowed, get medical help or contact the Poison Control center right away.

Directions

- Use on wipe per object to avoid cross contamination
- Allow to dry without wiping
- Discard wipe in trash receptacle after use
- Do not flush
- For dispensing, peel back front label at tab
- Remove towelettes as needed
- Reseal pouch by pressing label firmly back into place

Other information

- Store below 104 °F (40 °C)
- May discolor certain fabrics.

Inactive ingredients

Glycerin, Water.